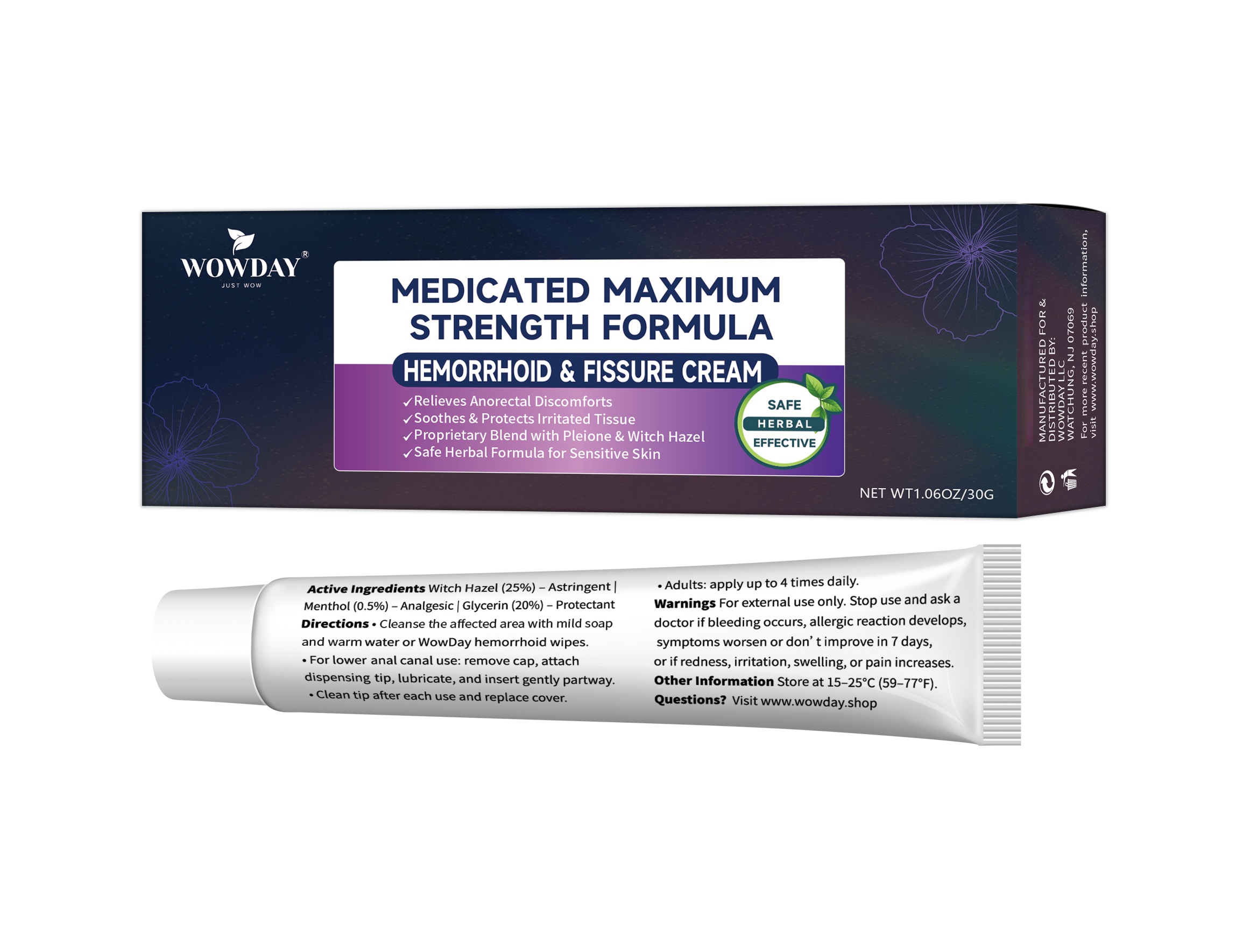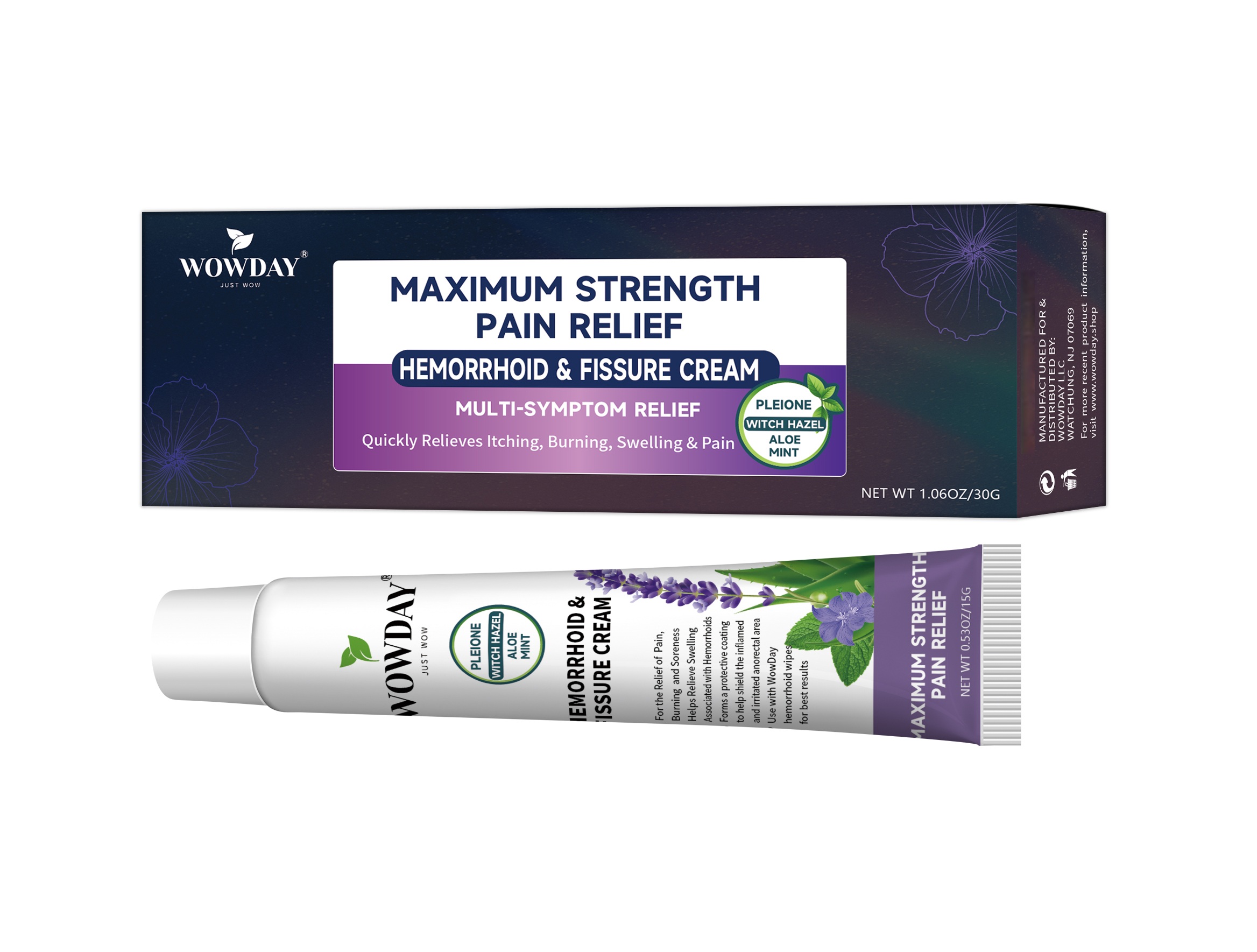 DRUG LABEL: WowDay Hemorrhoid and Fissure Cream
NDC: 87113-1008 | Form: CREAM
Manufacturer: WowDay LLC
Category: otc | Type: HUMAN OTC DRUG LABEL
Date: 20260212

ACTIVE INGREDIENTS: WITCH HAZEL 3.75 g/15 g; GLYCERIN 3 g/15 g; MENTHOL 0.075 g/15 g
INACTIVE INGREDIENTS: ETHYLPARABEN; EPIDIHYDROCHOLESTERIN; LIMONENE, (+)-; ALOE VERA LEAF POLYSACCHARIDES; MENTHOL PROPYLENE GLYCOL CARBONATE, (-)-; ALOE EMODIN; CITRIC ACID MONOHYDRATE; VITAMIN A; VITAMIN K-DEPENDENT PROTEIN C; 4'-DEMETHYLEPIPODOFILOX BENZYLIDENE GLYCOSIDE; GLUCOMANNAN; VITAMIN E POLYETHYLENE GLYCOL SUCCINATE; MINERAL OIL; CARBOMER; ISOGLYCYRRHIZINIC ACID; MIMOSINE; COLCHICINE

DOSAGE AND ADMINISTRATION

- cleanse the affected area with mild soap and warm water, rinse thoroughly, and then gently dry (patting or blotting) with tissue or soft cloth
- for application in the lower anal canal: remove cover from dispensing cap, attach dispensing cap to tube, lubricate well, then gently insert dispensing cap partway into the anus
- thoroughly cleanse dispensing cap after each use and replace cover
- children under 12 years of age consult your pediatrician
- adults: apply to the affected area up to 4 times daily, especially at night, in the morning or after each bowel movement

Keep out of reach of children.

If swallowed, get medical help or contact a Poison Control Center right away.

Stop use and ask a doctor if

* bleeding occurs

* an allergic reaction develops

* condition worsens or does not improve within seven days

* the symptom being treated does not subside or if redness, iritation, swelling, pain or other symptoms develop or increase

Ask a doctor/pharmacist before use if you are

* presently taking a prescription drug for high blood pressure or depression

* pregnant or breast-feeding

Ask a doctor before use if you have

* heart disease * diabetes

* thyroid disease * high blood pressure

* difficulty in urination due to enlargement of the prostate gland

* allergies to any of the components of this product

PURPOSE

- temporarily shrinks hemorrhoidal tissue
- temporarily relieves pain, soreness, or burning
- helps relieve the local itching and discomfort associated with hemorrhoids
- temporarily provides a coating for relief of anorectal discomforts
- temporarily protects the inflamed, irritated anorectal surface to help make bowel movements less painful

WARNINGS

- for external use only
- when using finger cots or an applicator, apply externally or to the skin of the anal canal only
- do not put this product into the rectum

ACTIVE INGREDIENT

Witch Hazel (25%) ……… Astringent

Menthol (0.5%) …………. Analgesic

Glycerin (20%) …………… Protectant

Questions or comments?
Email: wowday4u@gmail.com

INACTIVE INGREDIENT

Vitamin A、 C、E, Citric Acid Monohydrate, Isoglycyrrhizinic acid, Mimosine, Epidihydrocholesterin, Colchicine, Mineral Oil, Glucomannan, Aloe-emodin, 4'-Demethylepipodofilox Benzylidene Glycoside, Aloe Vera Leaf Polysaccharides, Limonene, Carbomer, Menthol Propylene Glycol Carbonate, Ethylparaben

INDICATIONS AND USAGE

- temporarily shrinks hemorrhoidal tissue
- temporarily relieves pain, soreness, or burning
- helps relieve the local itching and discomfort associated with hemorrhoids
- temporarily provides a coating for relief of anorectal discomforts
- temporarily protects the inflamed, irritated anorectal surface to help make bowel movements less painful